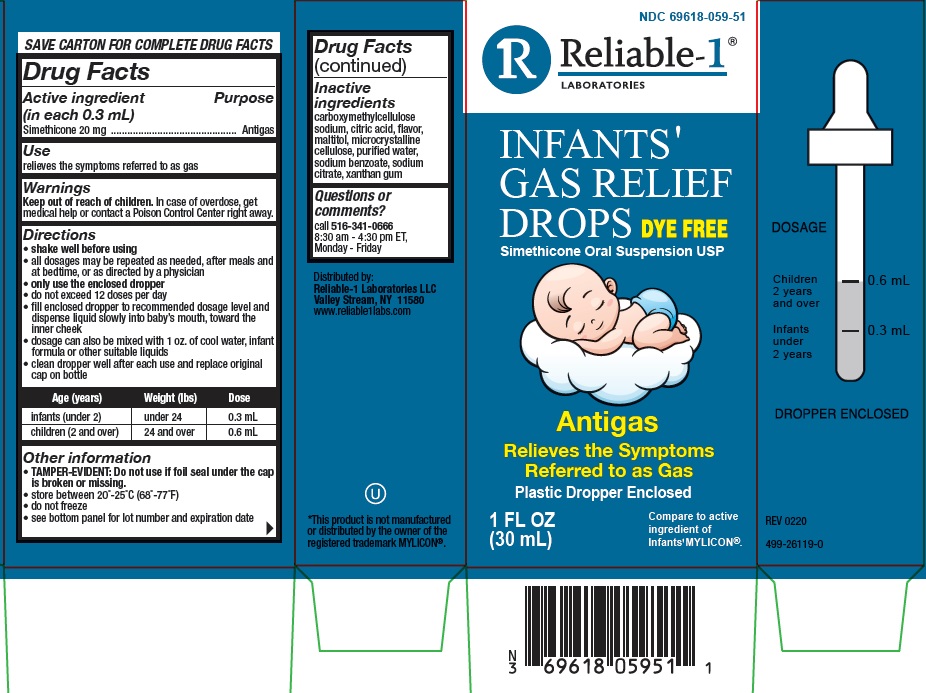 DRUG LABEL: INFANTS GAS RELIEF DROPS
NDC: 69618-059 | Form: SUSPENSION/ DROPS
Manufacturer: RELIABLE 1 LABORATORIES
Category: otc | Type: HUMAN OTC DRUG LABEL
Date: 20231107

ACTIVE INGREDIENTS: DIMETHICONE 20 mg/0.3 mL
INACTIVE INGREDIENTS: CARBOXYMETHYLCELLULOSE SODIUM; ANHYDROUS CITRIC ACID; MALTITOL; CELLULOSE, MICROCRYSTALLINE; WATER; SODIUM BENZOATE; SODIUM CITRATE; XANTHAN GUM

REL infant drops

Active ingredient (in each 0.3 mL)

Simethicone 20 mg

Purpose

Antigas

Use

relieves the symptoms referred to as gas

Warnings

Keep out of reach of children. In case of overdose, get medical help or contact a poison control center right away.

Directions

- shake well before using
- all dosages may be repeated as needed, after meals and at bedtime, or as directed by a physician
- only use the enclosed dropper
- do not exceed 12 doses per day
- fill enclosed dropper to recommended dosage level and dispense liquid slowly into baby’s mouth, toward the inner cheek
- dosage can also be mixed with 1 oz. of cool water, infant formula or other suitable liquids
- clean dropper well after each use and replace original cap on bottle

Age (years) | Weight (lbs) | Dose
infants (under 2) | under 24 | 0.3 mL
children (2 and over) | 24 and over | 0.6 mL

Other information

- TAMPER-EVIDENT: Do not use if foil seal under the cap is broken or missing.
- store between 20°-25°C (68°-77°F)
- do not freeze
- see bottom panel for lot number and expiration date

Inactive ingredients

carboxymethylcellulose sodium, citric acid, flavor, maltitol, microcrystalline cellulose, purified water, sodium benzoate, sodium citrate, xanthan gum.

Questions or comments?

call 516-341-0666
8:30 am - 4:30 pm ET,
Monday - Friday